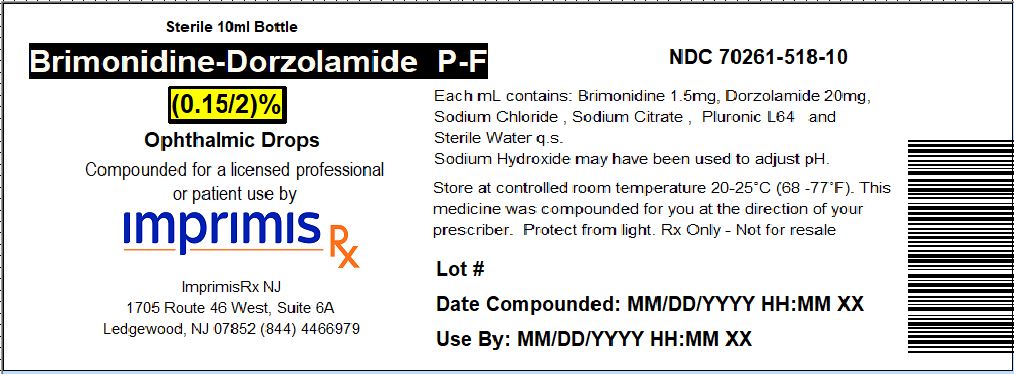 DRUG LABEL: Brim-Dor PF
NDC: 70261-518 | Form: SOLUTION/ DROPS
Manufacturer: ImprimisRx NJ
Category: prescription | Type: HUMAN PRESCRIPTION DRUG LABEL
Date: 20180508

ACTIVE INGREDIENTS: BRIMONIDINE TARTRATE 1.5 mg/1 mL; DORZOLAMIDE HYDROCHLORIDE 20 mg/1 mL

STORAGE AND HANDLING

Store at 20° to 25° C (68° to 77° F)